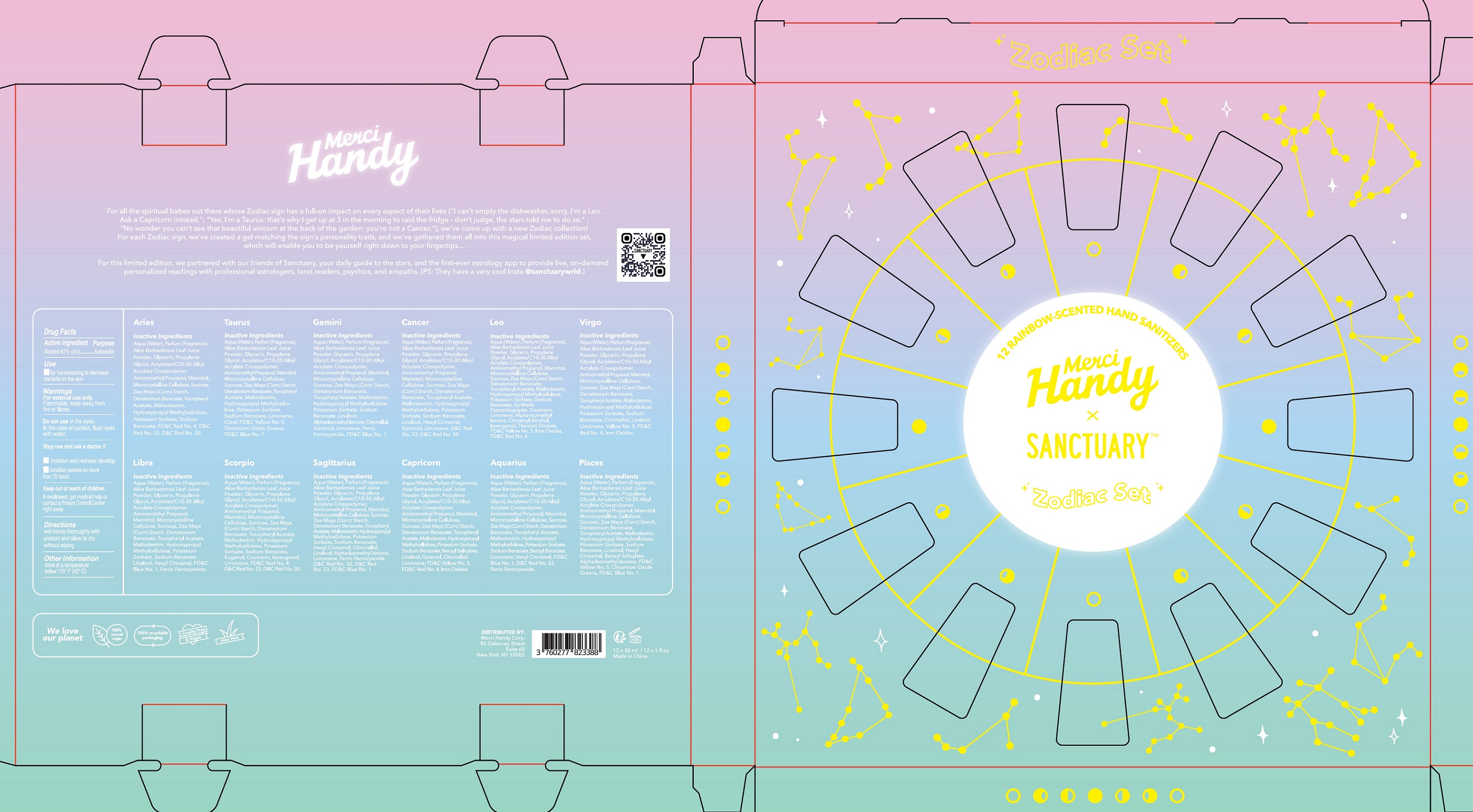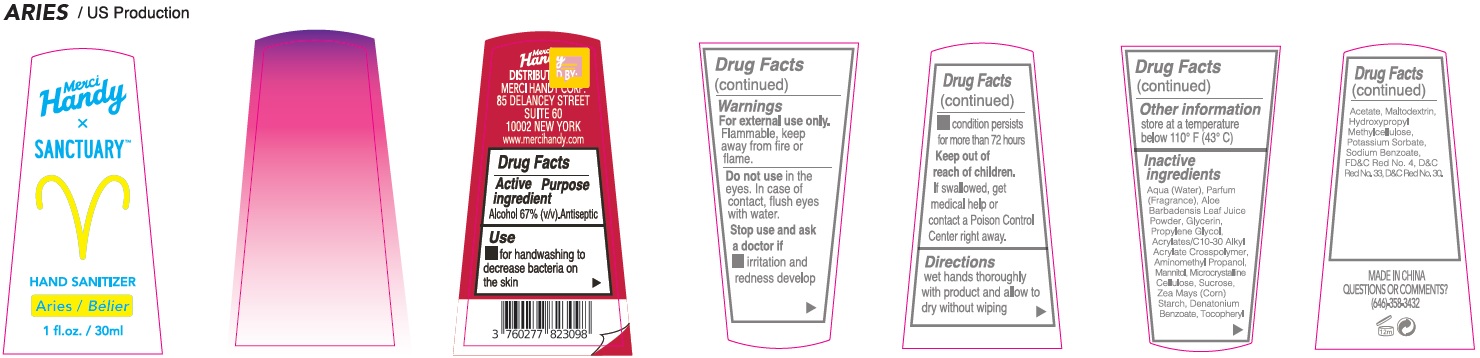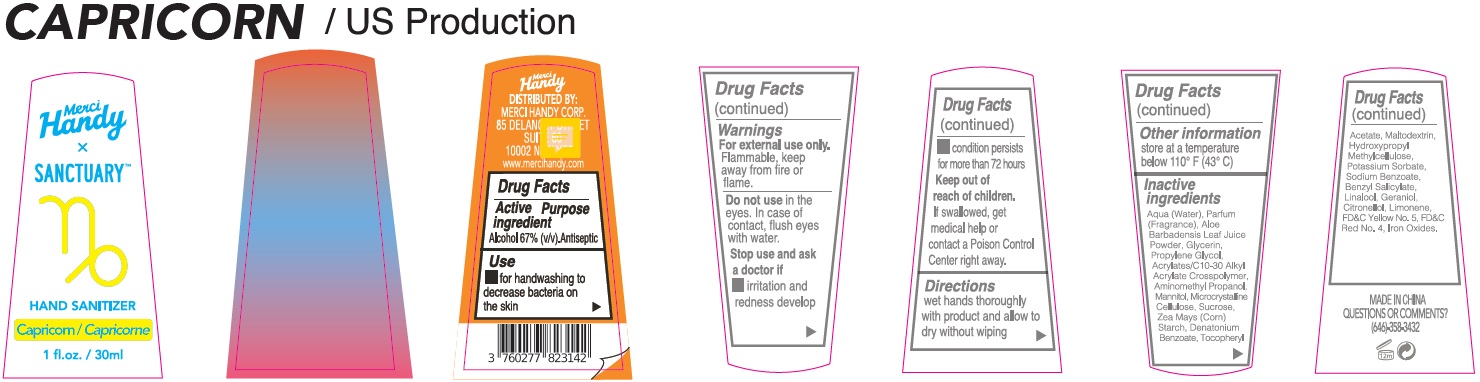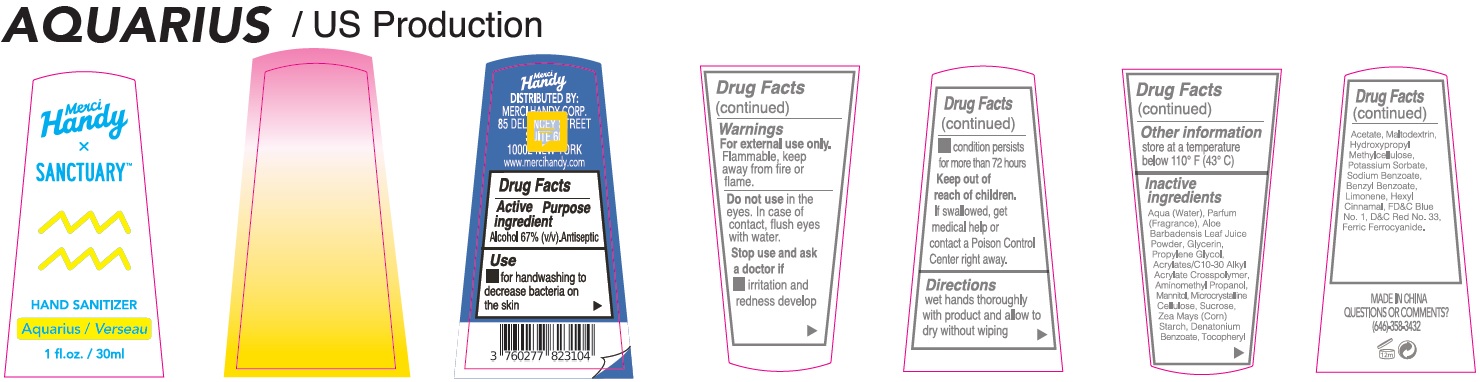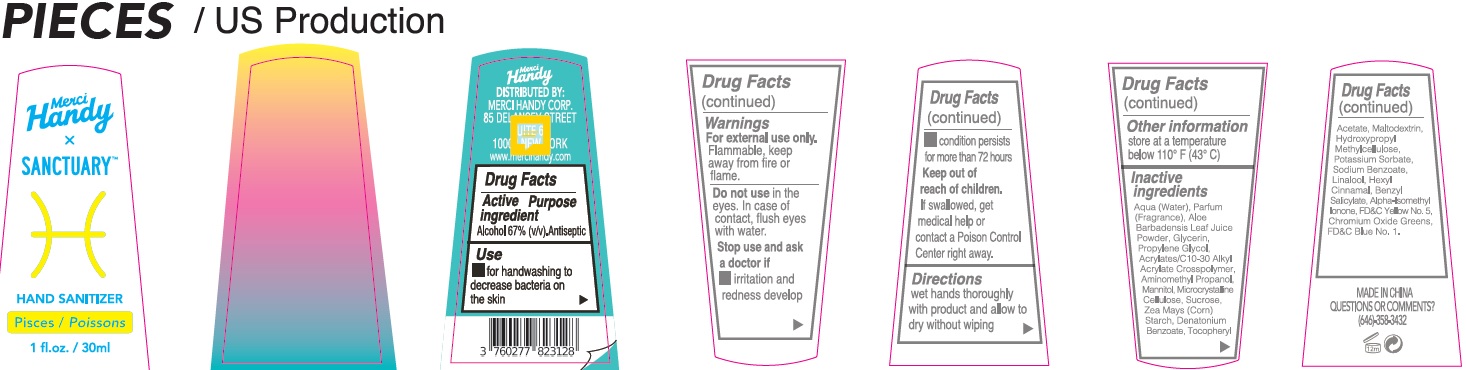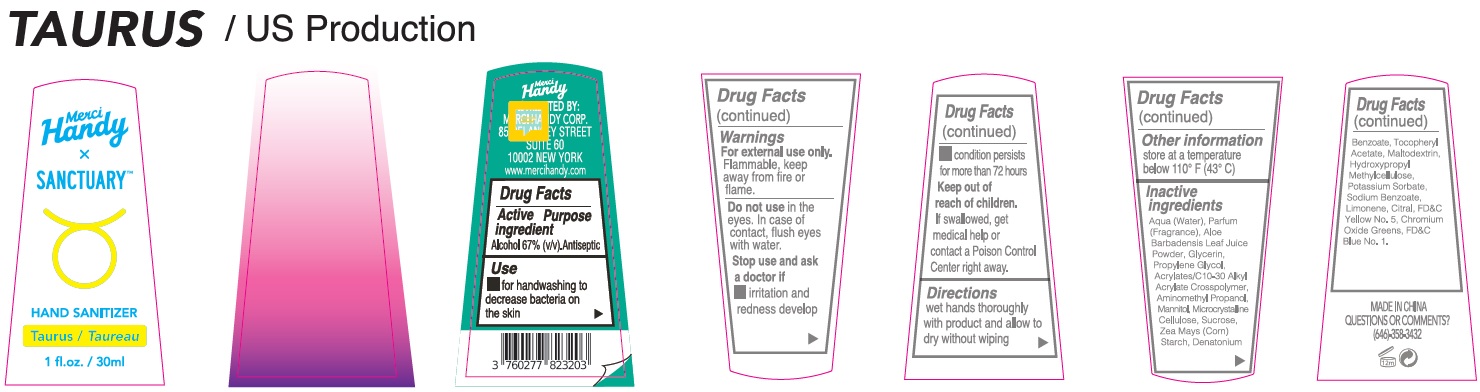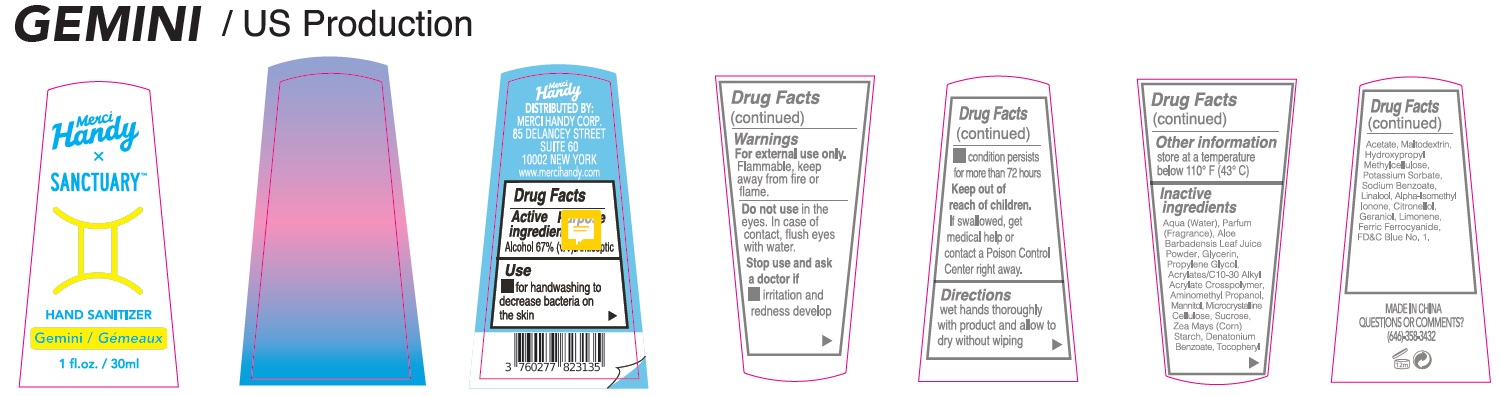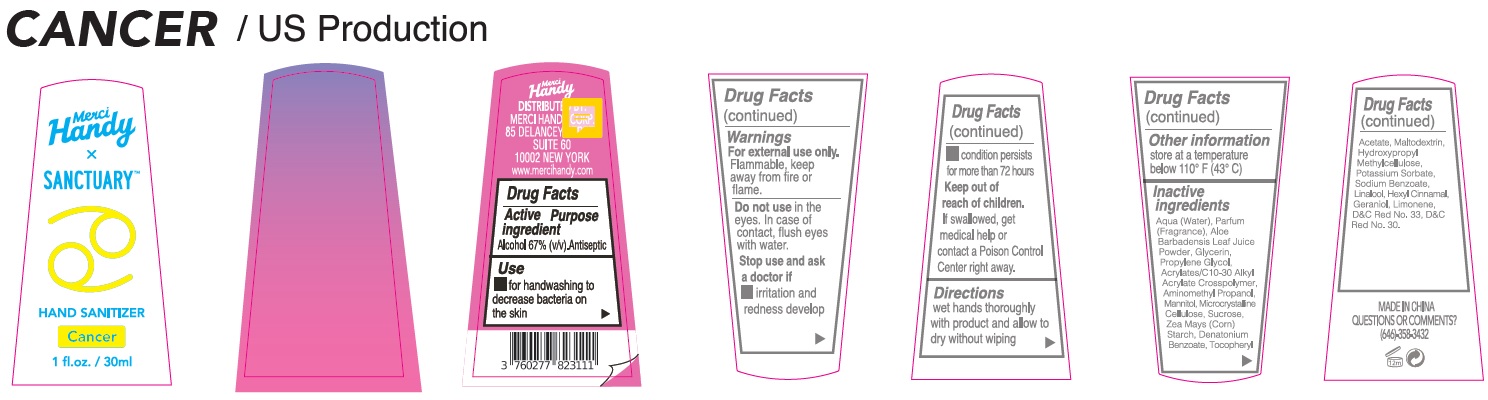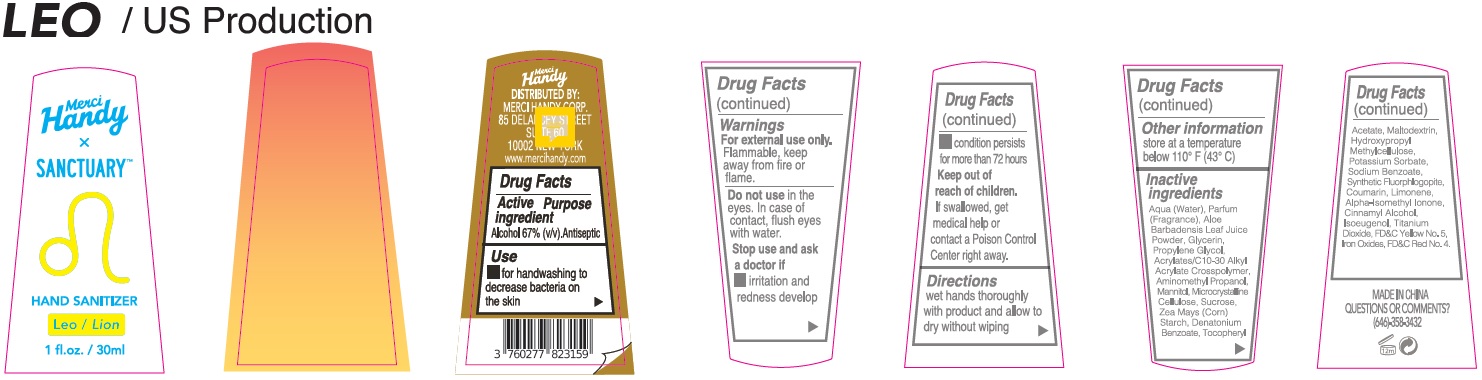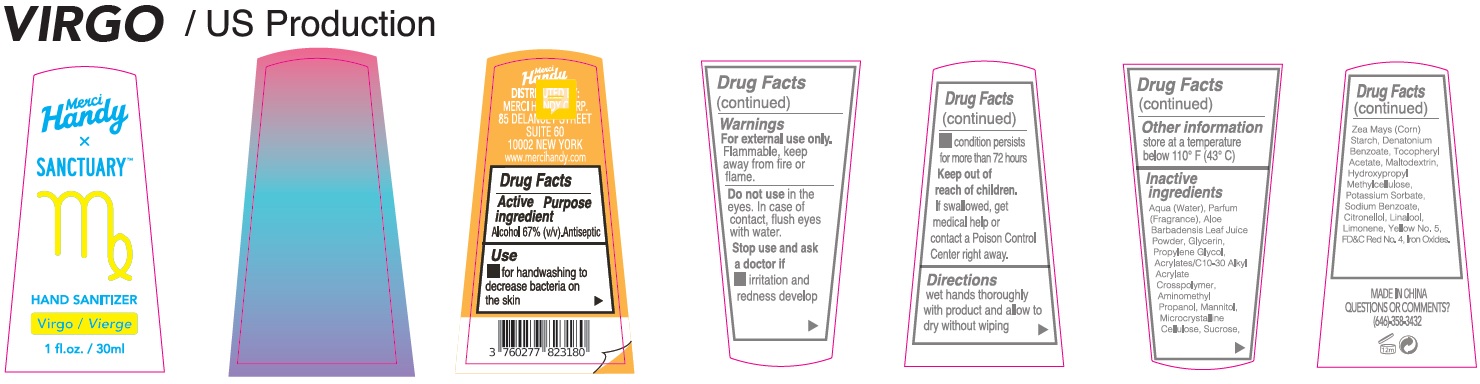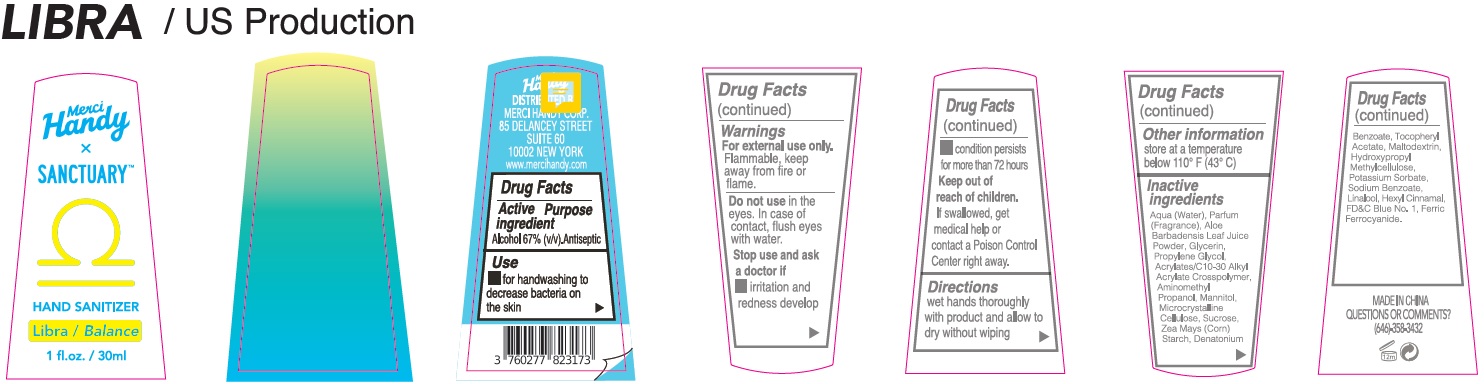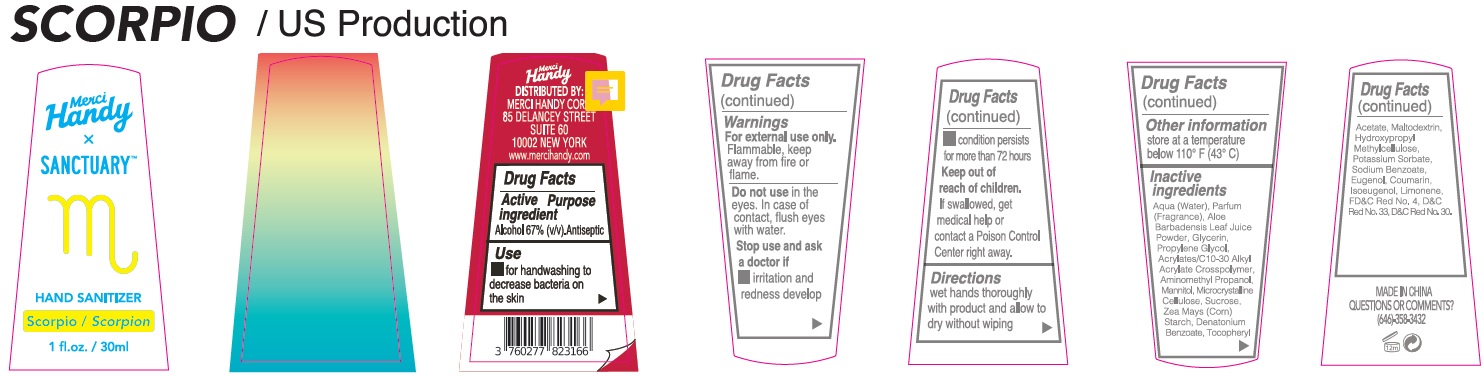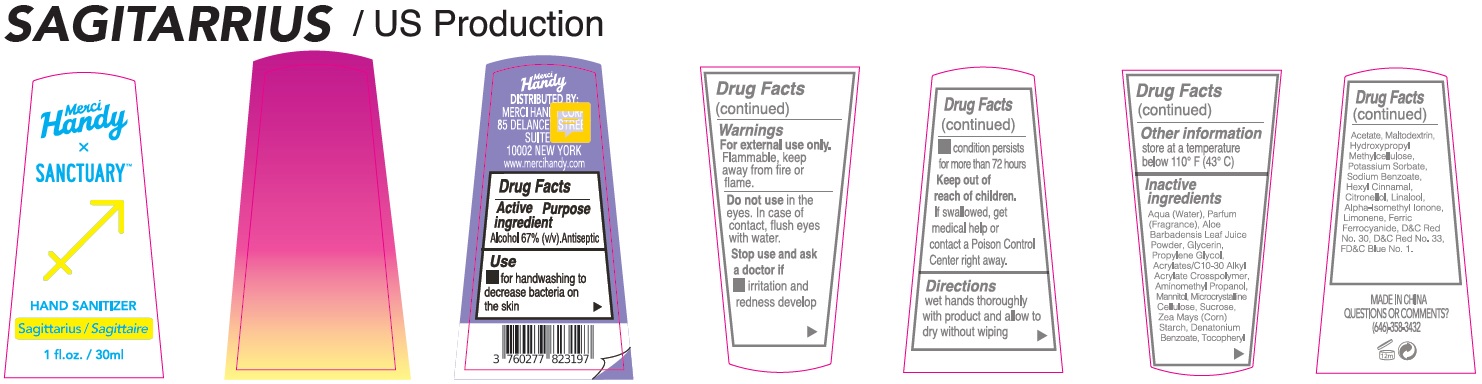 DRUG LABEL: Merci Handy Sanctuary Hand Sanitizer ZODIAC SET
NDC: 72866-017 | Form: KIT | Route: TOPICAL
Manufacturer: MERCI HANDY CORPORATION
Category: otc | Type: HUMAN OTC DRUG LABEL
Date: 20240123

ACTIVE INGREDIENTS: ALCOHOL 67 mL/100 mL; ALCOHOL 67 mL/100 mL; ALCOHOL 67 mL/100 mL; ALCOHOL 67 mL/100 mL; ALCOHOL 67 mL/100 mL; ALCOHOL 67 mL/100 mL; ALCOHOL 67 mL/100 mL; ALCOHOL 67 mL/100 mL; ALCOHOL 67 mL/100 mL; ALCOHOL 67 mL/100 mL; ALCOHOL 67 mL/100 mL; ALCOHOL 67 mL/100 mL
INACTIVE INGREDIENTS: WATER; ALOE VERA LEAF; GLYCERIN; PROPYLENE GLYCOL; CARBOMER INTERPOLYMER TYPE A (ALLYL SUCROSE CROSSLINKED); AMINOMETHYLPROPANOL; MANNITOL; MICROCRYSTALLINE CELLULOSE; SUCROSE; CORN; DENATONIUM BENZOATE; .ALPHA.-TOCOPHEROL ACETATE; MALTODEXTRIN; HYPROMELLOSE, UNSPECIFIED; POTASSIUM SORBATE; SODIUM BENZOATE; FD&C RED NO. 4; D&C RED NO. 33; D&C RED NO. 30; WATER; ALOE VERA LEAF; GLYCERIN; PROPYLENE GLYCOL; CARBOMER INTERPOLYMER TYPE A (ALLYL SUCROSE CROSSLINKED); AMINOMETHYLPROPANOL; MANNITOL; MICROCRYSTALLINE CELLULOSE; SUCROSE; CORN; DENATONIUM BENZOATE; .ALPHA.-TOCOPHEROL ACETATE; MALTODEXTRIN; HYPROMELLOSE, UNSPECIFIED; POTASSIUM SORBATE; SODIUM BENZOATE; LIMONENE, (+)-; CITRAL; FD&C YELLOW NO. 5; CHROMIC OXIDE; FD&C BLUE NO. 1; WATER; ALOE VERA LEAF; GLYCERIN; PROPYLENE GLYCOL; CARBOMER INTERPOLYMER TYPE A (ALLYL SUCROSE CROSSLINKED); AMINOMETHYLPROPANOL; MANNITOL; MICROCRYSTALLINE CELLULOSE; SUCROSE; CORN; DENATONIUM BENZOATE; .ALPHA.-TOCOPHEROL ACETATE; MALTODEXTRIN; HYPROMELLOSE, UNSPECIFIED; POTASSIUM SORBATE; SODIUM BENZOATE; LINALOOL, (+/-)-; ISOMETHYL-.ALPHA.-IONONE; .BETA.-CITRONELLOL, (R)-; GERANIOL; LIMONENE, (+)-; FERRIC FERROCYANIDE; FD&C BLUE NO. 1; WATER; ALOE VERA LEAF; GLYCERIN; PROPYLENE GLYCOL; CARBOMER INTERPOLYMER TYPE A (ALLYL SUCROSE CROSSLINKED); AMINOMETHYLPROPANOL; MANNITOL; MICROCRYSTALLINE CELLULOSE; SUCROSE; CORN; DENATONIUM BENZOATE; .ALPHA.-TOCOPHEROL ACETATE; MALTODEXTRIN; HYPROMELLOSE, UNSPECIFIED; POTASSIUM SORBATE; SODIUM BENZOATE; LINALOOL, (+/-)-; .ALPHA.-HEXYLCINNAMALDEHYDE; GERANIOL; LIMONENE, (+)-; D&C RED NO. 33; D&C RED NO. 30; WATER; ALOE VERA LEAF; GLYCERIN; PROPYLENE GLYCOL; CARBOMER INTERPOLYMER TYPE A (ALLYL SUCROSE CROSSLINKED); AMINOMETHYLPROPANOL; MANNITOL; MICROCRYSTALLINE CELLULOSE; SUCROSE; CORN; DENATONIUM BENZOATE; .ALPHA.-TOCOPHEROL ACETATE; MALTODEXTRIN; HYPROMELLOSE, UNSPECIFIED; POTASSIUM SORBATE; SODIUM BENZOATE; MAGNESIUM POTASSIUM ALUMINOSILICATE FLUORIDE; COUMARIN; LIMONENE, (+)-; .ALPHA.-HEXYLCINNAMALDEHYDE; CINNAMYL ALCOHOL; ISOEUGENOL; TITANIUM DIOXIDE; FD&C YELLOW NO. 5; FERRIC OXIDE RED; FD&C RED NO. 4; WATER; ALOE VERA LEAF; GLYCERIN; PROPYLENE GLYCOL; CARBOMER INTERPOLYMER TYPE A (ALLYL SUCROSE CROSSLINKED); AMINOMETHYLPROPANOL; MANNITOL; MICROCRYSTALLINE CELLULOSE; SUCROSE; CORN; DENATONIUM BENZOATE; .ALPHA.-TOCOPHEROL ACETATE; MALTODEXTRIN; HYPROMELLOSE, UNSPECIFIED; POTASSIUM SORBATE; SODIUM BENZOATE; .BETA.-CITRONELLOL, (R)-; LINALOOL, (+/-)-; LIMONENE, (+)-; FD&C YELLOW NO. 5; FD&C RED NO. 4; FERRIC OXIDE RED; WATER; ALOE VERA LEAF; GLYCERIN; PROPYLENE GLYCOL; CARBOMER INTERPOLYMER TYPE A (ALLYL SUCROSE CROSSLINKED); AMINOMETHYLPROPANOL; MANNITOL; MICROCRYSTALLINE CELLULOSE; SUCROSE; CORN; DENATONIUM BENZOATE; .ALPHA.-TOCOPHEROL ACETATE; MALTODEXTRIN; HYPROMELLOSE, UNSPECIFIED; POTASSIUM SORBATE; SODIUM BENZOATE; LINALOOL, (+/-)-; .ALPHA.-HEXYLCINNAMALDEHYDE; FD&C BLUE NO. 1; FERRIC FERROCYANIDE; MALTODEXTRIN; HYPROMELLOSE, UNSPECIFIED; POTASSIUM SORBATE; SODIUM BENZOATE; EUGENOL; COUMARIN; ISOEUGENOL; LIMONENE, (+)-; FD&C RED NO. 4; D&C RED NO. 33; D&C RED NO. 30; WATER; ALOE VERA LEAF; GLYCERIN; PROPYLENE GLYCOL; CARBOMER INTERPOLYMER TYPE A (ALLYL SUCROSE CROSSLINKED); AMINOMETHYLPROPANOL; MANNITOL; MICROCRYSTALLINE CELLULOSE; SUCROSE; CORN; DENATONIUM BENZOATE; .ALPHA.-TOCOPHEROL ACETATE; WATER; ALOE VERA LEAF; GLYCERIN; PROPYLENE GLYCOL; CARBOMER INTERPOLYMER TYPE A (ALLYL SUCROSE CROSSLINKED); AMINOMETHYLPROPANOL; MANNITOL; MICROCRYSTALLINE CELLULOSE; SUCROSE; CORN; DENATONIUM BENZOATE; .ALPHA.-TOCOPHEROL ACETATE; MALTODEXTRIN; HYPROMELLOSE, UNSPECIFIED; POTASSIUM SORBATE; SODIUM BENZOATE; .ALPHA.-HEXYLCINNAMALDEHYDE; .BETA.-CITRONELLOL, (R)-; LINALOOL, (+/-)-; ISOMETHYL-.ALPHA.-IONONE; LIMONENE, (+)-; FERROCYANIDE ION; D&C RED NO. 33; FD&C BLUE NO. 1; WATER; ALOE VERA LEAF; GLYCERIN; PROPYLENE GLYCOL; CARBOMER INTERPOLYMER TYPE A (ALLYL SUCROSE CROSSLINKED); AMINOMETHYLPROPANOL; MANNITOL; MICROCRYSTALLINE CELLULOSE; SUCROSE; CORN; DENATONIUM BENZOATE; .ALPHA.-TOCOPHEROL ACETATE; MALTODEXTRIN; HYPROMELLOSE, UNSPECIFIED; POTASSIUM SORBATE; SODIUM BENZOATE; BENZYL SALICYLATE; LINALOOL, (+/-)-; GERANIOL; .BETA.-CITRONELLOL, (R)-; LIMONENE, (+)-; FD&C YELLOW NO. 5; FD&C RED NO. 4; FERRIC OXIDE RED; WATER; ALOE VERA LEAF; GLYCERIN; PROPYLENE GLYCOL; CARBOMER INTERPOLYMER TYPE A (ALLYL SUCROSE CROSSLINKED); AMINOMETHYLPROPANOL; MANNITOL; MICROCRYSTALLINE CELLULOSE; SUCROSE; CORN; DENATONIUM BENZOATE; .ALPHA.-TOCOPHEROL ACETATE; MALTODEXTRIN; HYPROMELLOSE, UNSPECIFIED; POTASSIUM SORBATE; SODIUM BENZOATE; BENZYL BENZOATE; LIMONENE, (+)-; .ALPHA.-HEXYLCINNAMALDEHYDE; FD&C BLUE NO. 1; D&C RED NO. 33; FERRIC FERROCYANIDE; WATER; ALOE VERA LEAF; GLYCERIN; PROPYLENE GLYCOL; CARBOMER INTERPOLYMER TYPE A (ALLYL SUCROSE CROSSLINKED); AMINOMETHYLPROPANOL; MANNITOL; MICROCRYSTALLINE CELLULOSE; SUCROSE; CORN; DENATONIUM BENZOATE; .ALPHA.-TOCOPHEROL ACETATE; MALTODEXTRIN; HYPROMELLOSE, UNSPECIFIED; POTASSIUM SORBATE; SODIUM BENZOATE; LINALOOL, (+/-)-; .ALPHA.-HEXYLCINNAMALDEHYDE; BENZYL SALICYLATE; ISOMETHYL-.ALPHA.-IONONE; FD&C YELLOW NO. 5; CHROMIC OXIDE; FD&C BLUE NO. 1

Merci Handy sanctuary Hand Sanitizer ZODIAC SET

Active ingredient

Alcohol 67% (v/v)

Purpose

Antiseptic

Use

- for handwashing to decrease bacteria on the skin

Warnings

For external use only.

Flammable keep away from fire or flame.

Do not use

in the eyes. In the case of contact, flush eyes with water.

Stop use and ask a doctor if

- irritation and redness develop
- condition persists for more than 72 hours

Keep out of reach of children

If swallowed, get medical help or contact a Poison Control Center right away

Directions

wet hands thoroughly with product and allow to dry without wiping

Other information

store at a temperature below 110° F (43° C)

Inactive Ingredients

Aqua (Water), Parfum (Fragrance), Aloe Barbadensis Leaf Juice Powder, Glycerin, Propylene Glycol, Acrylates/C10-30 Alkyl Acrylate Crosspolymer, Aminomethyl Propanol, Mannitol, Microcrystalline Cellulose, Sucrose, Zea Mays (Corn) Starch, Denatonium Benzoate, Tocopheryl Acetate, Maltodextrin, Hydroxypropyl Methylcellulose, Potassium Sorbate, Sodium Benzoate, FD&C Red No.4, D&C Red No.33, D&C Red No.30

QUESTIONS OR COMMENTS?

(646)-358-3432

Active ingredient

Alcohol 67% (v/v)

Purpose

Antiseptic

Use

- for handwashing to decrease bacteria on the skin

Warnings

For external use only.

Flammable keep away from fire or flame.

Do not use

in the eyes. In the case of contact, flush eyes with water.

Stop use and ask a doctor if

- irritation and redness develop
- condition persists for more than 72 hours

Keep out of reach of children

If swallowed, get medical help or contact a Poison Control Center right away

Directions

wet hands thoroughly with product and allow to dry without wiping

Other information

store at a temperature below 110° F (43° C)

Inactive Ingredients

Aqua (Water), Parfum (Fragrance), Aloe Barbadensis Leaf Juice Powder, Glycerin, Propylene Glycol, Acrylates/C10-30 Alkyl Acrylate Crosspolymer, Aminomethyl Propanol, Mannitol, Microcrystalline Cellulose, Sucrose, Zea Mays (Corn) Starch, Denatonium Benzoate, Tocopheryl Acetate, Maltodextrin, Hydroxypropyl Methylcellulose, Potassium Sorbate, Sodium Benzoate, Limonene, Citral, FD&C Yellow No. 5, Chromium Oxide Greens, FD&C Blue No.1.

QUESTIONS OR COMMENTS?

(646)-358-3432

Active ingredient

Alcohol 67% (v/v)

Purpose

Antiseptic

Use

- for handwashing to decrease bacteria on the skin

Warnings

For external use only.

Flammable keep away from fire or flame.

Do not use

in the eyes. In the case of contact, flush eyes with water.

Stop use and ask a doctor if

- irritation and redness develop
- condition persists for more than 72 hours

Keep out of reach of children

If swallowed, get medical help or contact a Poison Control Center right away

Directions

wet hands thoroughly with product and allow to dry without wiping

Other information

store at a temperature below 110° F (43° C)

Inactive Ingredients

Aqua (Water), Parfum (Fragrance), Aloe Barbadensis Leaf Juice Powder, Glycerin, Propylene Glycol, Acrylates/C10-30 Alkyl Acrylate Crosspolymer, Aminomethyl Propanol, Mannitol, Microcrystalline Cellulose, Sucrose, Zea Mays (Corn) Starch, Denatonium Benzoate, Tocopheryl Acetate, Maltodextrin, Hydroxypropyl Methylcellulose, Potassium Sorbate, Sodium Benzoate, Linalool, Alpha-Isomethyl Ionone, Citronellol, Geraniol, Limonene, Ferric Ferrocyanide, FD&C Blue No.1

QUESTIONS OR COMMENTS?

(646)-358-3432

Active ingredient

Alcohol 67% (v/v)

Purpose

Antiseptic

Use

- for handwashing to decrease bacteria on the skin

Warnings

For external use only.

Flammable keep away from fire or flame.

Do not use

in the eyes. In the case of contact, flush eyes with water.

Stop use and ask a doctor if

- irritation and redness develop
- condition persists for more than 72 hours

Keep out of reach of children

If swallowed, get medical help or contact a Poison Control Center right away

Directions

wet hands thoroughly with product and allow to dry without wiping

Other information

store at a temperature below 110° F (43° C)

Inactive Ingredients

Aqua (Water), Parfum (Fragrance), Aloe Barbadensis Leaf Juice Powder, Glycerin, Propylene Glycol, Acrylates/C10-30 Alkyl Acrylate Crosspolymer, Aminomethyl Propanol, Mannitol, Microcrystalline Cellulose, Sucrose, Zea Mays (Corn) Starch, Denatonium Benzoate, Tocopheryl Acetate, Maltodextrin, Hydroxypropyl Methylcellulose, Potassium Sorbate, Sodium Benzoate, Linalool, Hexyl Cinnamal, Geraniol, Limonene, D&C Red No.33, D&C Red No.30

QUESTIONS OR COMMENTS?

(646)-358-3432

Active ingredient

Alcohol 67% (v/v)

Purpose

Antiseptic

Use

- for handwashing to decrease bacteria on the skin

Warnings

For external use only.

Flammable keep away from fire or flame.

Do not use

in the eyes. In the case of contact, flush eyes with water.

Stop use and ask a doctor if

- irritation and redness develop
- condition persists for more than 72 hours

Keep out of reach of children

If swallowed, get medical help or contact a Poison Control Center right away

Directions

wet hands thoroughly with product and allow to dry without wiping

Other information

store at a temperature below 110° F (43° C)

Inactive Ingredients

Aqua (Water), Parfum (Fragrance), Aloe Barbadensis Leaf Juice Powder, Glycerin, Propylene Glycol, Acrylates/C10-30 Alkyl Acrylate Crosspolymer, Aminomethyl Propanol, Mannitol, Microcrystalline Cellulose, Sucrose, Zea Mays (Corn) Starch, Denatonium Benzoate, Tocopheryl Acetate, Maltodextrin, Hydroxypropyl Methylcellulose, Potassium Sorbate, Sodium Benzoate, Synthetic Fluorphlogopite, Coumarin, Limonene, Alpha-Isomethyl Ionone, Cinnamyl Alcohol, Isoeugenol, Titanium Dioxide, FD&C Yellow No. 5, Iron Oxides, FD&C Red No. 4.

QUESTIONS OR COMMENTS?

(646)-358-3432

Active ingredient

Alcohol 67% (v/v)

Purpose

Antiseptic

Use

- for handwashing to decrease bacteria on the skin

Warnings

For external use only.

Flammable keep away from fire or flame.

Do not use

in the eyes. In the case of contact, flush eyes with water.

Stop use and ask a doctor if

- irritation and redness develop
- condition persists for more than 72 hours

Keep out of reach of children

If swallowed, get medical help or contact a Poison Control Center right away

Directions

wet hands thoroughly with product and allow to dry without wiping

Other information

store at a temperature below 110° F (43° C)

Inactive Ingredients

Aqua (Water), Parfum (Fragrance), Aloe Barbadensis Leaf Juice Powder, Glycerin, Propylene Glycol, Acrylates/C10-30 Alkyl Acrylate Crosspolymer, Aminomethyl Propanol, Mannitol, Microcrystalline Cellulose, Sucrose, Zea Mays (Corn) Starch, Denatonium Benzoate, Tocopheryl Acetate, Maltodextrin, Hydroxypropyl Methylcellulose, Potassium Sorbate, Sodium Benzoate, Citronellol, Linalool, Limonene, Yellow No. 5, FD&C Red No. 4, Iron Oxides.

QUESTIONS OR COMMENTS?

(646)-358-3432

Active ingredient

Alcohol 67% (v/v)

Purpose

Antiseptic

Use

- for handwashing to decrease bacteria on the skin

Warnings

For external use only.

Flammable keep away from fire or flame.

Do not use

in the eyes. In the case of contact, flush eyes with water.

Stop use and ask a doctor if

- irritation and redness develop
- condition persists for more than 72 hours

Keep out of reach of children

If swallowed, get medical help or contact a Poison Control Center right away

Directions

wet hands thoroughly with product and allow to dry without wiping

Other information

store at a temperature below 110° F (43° C)

Inactive Ingredients

Aqua (Water), Parfum (Fragrance), Aloe Barbadensis Leaf Juice Powder, Glycerin, Propylene Glycol, Acrylates/C10-30 Alkyl Acrylate Crosspolymer, Aminomethyl Propanol, Mannitol, Microcrystalline Cellulose, Sucrose, Zea Mays (Corn) Starch, Denatonium Benzoate, Tocopheryl Acetate, Maltodextrin, Hydroxypropyl Methylcellulose, Potassium Sorbate, Sodium Benzoate, Linalool, Hexyl Cinnamal, FD&C Blue No. 1, Ferric Ferrocyanide.

QUESTIONS OR COMMENTS?

(646)-358-3432

Active ingredient

Alcohol 67% (v/v)

Purpose

Antiseptic

Use

- for handwashing to decrease bacteria on the skin

Warnings

For external use only.
Flammable keep away from fire or flame.

Do not use

in the eyes. In the case of contact, flush eyes with water.

Stop use anKeep out of reach of childrend ask a doctor if

- irritation and redness develop
- condition persists for more than 72 hours

Keep out of reach of children

If swallowed, get medical help or contact a Poison Control Center right away

Directions

wet hands thoroughly with product and allow to dry without wiping

Other information

store at a temperature below 110° F (43° C)

Inactive Ingredients

Aqua (Water), Parfum (Fragrance), Aloe Barbadensis Leaf Juice Powder, Glycerin, Propylene Glycol, Acrylates/C10-30 Alkyl Acrylate Crosspolymer, Aminomethyl Propanol, Mannitol, Microcrystalline Cellulose, Sucrose, Zea Mays (Corn) Starch, Denatonium Benzoate, Tocopheryl Acetate, Maltodextrin, Hydroxypropyl Methylcellulose, Potassium Sorbate, Sodium Benzoate, Eugenol, Coumarin, Isoeugenol, Limonene, FD&C Red No. 4, D&C Red No. 33, D&C Red No. 30.

QUESTIONS OR COMMENTS?

(646)-358-3432

Active ingredient

Alcohol 67% (v/v)

Purpose

Antiseptic

Use

- for handwashing to decrease bacteria on the skin

Warnings

For external use only.

Flammable keep away from fire or flame.

Do not use

in the eyes. In the case of contact, flush eyes with water.

Stop use and ask a doctor if

- irritation and redness develop
- condition persists for more than 72 hours

Keep out of reach of children

If swallowed, get medical help or contact a Poison Control Center right away

Directions

wet hands thoroughly with product and allow to dry without wiping

Other information

store at a temperature below 110° F (43° C)

Inactive Ingredients

Aqua (Water), Parfum (Fragrance), Aloe Barbadensis Leaf Juice Powder, Glycerin, Propylene Glycol, Acrylates/C10-30 Alkyl Acrylate Crosspolymer, Aminomethyl Propanol, Mannitol, Microcrystalline Cellulose, Sucrose, Zea Mays (Corn) Starch, Denatonium Benzoate, Tocopheryl Acetate, Maltodextrin, Hydroxypropyl Methylcellulose, Potassium Sorbate, Sodium Benzoate, Hexyl Cinnamal, Citronellol, Linalool, Alpha-Isomethyl Ionone, Limonene, Ferrocyanide, D&C Red No. 33, FD&C Blue No. 1.

QUESTIONS OR COMMENTS?

(646)-358-3432

Active ingredient

Alcohol 67% (v/v)

Purpose

Antiseptic

Use

- for handwashing to decrease bacteria on the skin

Warnings

For external use only.

Flammable keep away from fire or flame.

Do not use

in the eyes. In the case of contact, flush eyes with water.

Stop use and ask a doctor if

- irritation and redness develop
- condition persists for more than 72 hours

Keep out of reach of children

If swallowed, get medical help or contact a Poison Control Center right away

Directions

wet hands thoroughly with product and allow to dry without wiping

Other information

store at a temperature below 110° F (43° C)

Inactive Ingredients

Aqua (Water), Parfum (Fragrance), Aloe Barbadensis Leaf Juice Powder, Glycerin, Propylene Glycol, Acrylates/C10-30 Alkyl Acrylate Crosspolymer, Aminomethyl Propanol, Mannitol, Microcrystalline Cellulose, Sucrose, Zea Mays (Corn) Starch, Denatonium Benzoate, Tocopheryl Acetate, Maltodextrin, Hydroxypropyl Methylcellulose, Potassium Sorbate, Sodium Benzoate, Benzyl Salicylate, Linalool, Geraniol, Citronellol, Limonene, FD&C Yellow No. 5, FD&C Red No. 4, Iron Oxides.

QUESTIONS OR COMMENTS?

(646)-358-3432

Active ingredient

Alcohol 67% (v/v)

Purpose

Antiseptic

Use

- for handwashing to decrease bacteria on the skin

Warnings

For external use only.

Flammable keep away from fire or flame.

Do not use

in the eyes. In the case of contact, flush eyes with water.

Stop use and ask a doctor if

- irritation and redness develop
- condition persists for more than 72 hours

Keep out of reach of children

If swallowed, get medical help or contact a Poison Control Center right away

Directions

wet hands thoroughly with product and allow to dry without wiping

Other information

store at a temperature below 110° F (43° C)

Inactive Ingredients

Aqua (Water), Parfum (Fragrance), Aloe Barbadensis Leaf Juice Powder, Glycerin, Propylene Glycol, Acrylates/C10-30 Alkyl Acrylate Crosspolymer, Aminomethyl Propanol, Mannitol, Microcrystalline Cellulose, Sucrose, Zea Mays (Corn) Starch, Denatonium Benzoate, Tocopheryl Acetate, Maltodextrin, Hydroxypropyl Methylcellulose, Potassium Sorbate, Sodium Benzoate, Benzyl Benzoate, Limonene, Hexyl Cinnamal, FD&C Blue No. 1, D&C Red No. 33, Ferric Ferrocyanide.

QUESTIONS OR COMMENTS?

(646)-358-3432

Active ingredient

Alcohol 67% (v/v)

Purpose

Antiseptic

Use

- for handwashing to decrease bacteria on the skin

Warnings

For external use only.

Flammable keep away from fire or flame.

Do not use

in the eyes. In the case of contact, flush eyes with water.

Stop use and ask a doctor if

- irritation and redness develop
- condition persists for more than 72 hours

Keep out of reach of children

If swallowed, get medical help or contact a Poison Control Center right away

Directions

wet hands thoroughly with product and allow to dry without wiping

Other information

store at a temperature below 110° F (43° C)

Inactive Ingredients

Aqua (Water), Parfum (Fragrance), Aloe Barbadensis Leaf Juice Powder, Glycerin, Propylene Glycol, Acrylates/C10-30 Alkyl Acrylate Crosspolymer, Aminomethyl Propanol, Mannitol, Microcrystalline Cellulose, Sucrose, Zea Mays (Corn) Starch, Denatonium Benzoate, Tocopheryl Acetate, Maltodextrin, Hydroxypropyl Methylcellulose, Potassium Sorbate, Sodium Benzoate, Linalool, Hexyl Cinnamal, Benzyl Salicylate, Alpha-Isomethyl Ionone, FD&C Yellow No. 5, Chromium Oxide Greens, FD&C Blue No. 1.

QUESTIONS OR COMMENTS?

(646)-358-3432